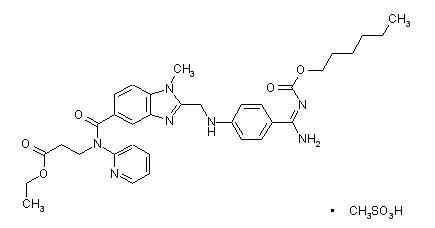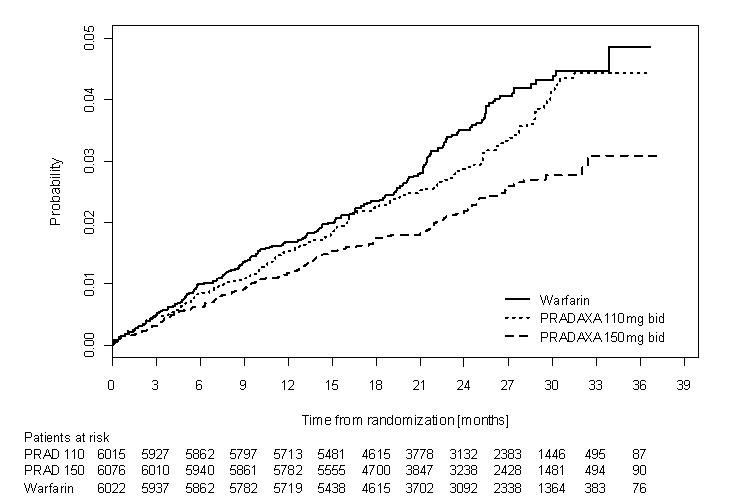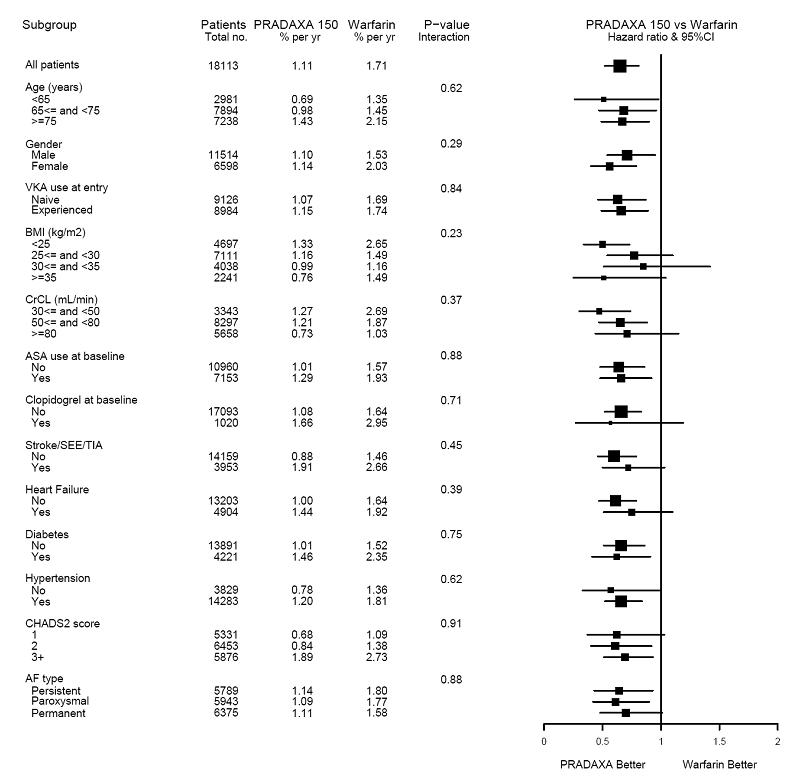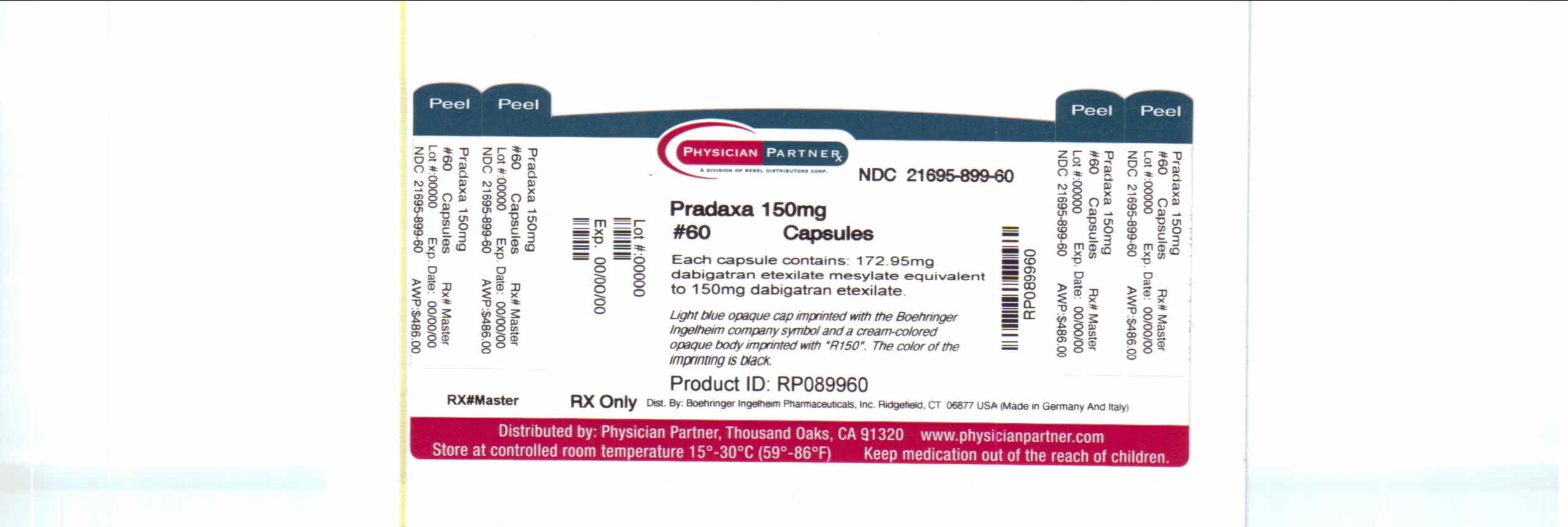 DRUG LABEL: PRADAXA
NDC: 21695-899 | Form: CAPSULE
Manufacturer: Rebel Distributors Corp
Category: prescription | Type: HUMAN PRESCRIPTION DRUG LABEL
Date: 20101123

ACTIVE INGREDIENTS: dabigatran etexilate mesylate 150 mg/1 1
INACTIVE INGREDIENTS: ACACIA; DIMETHICONE; HYPROMELLOSES; HYDROXYPROPYL CELLULOSE; TALC; TARTARIC ACID; CARRAGEENAN; FD&C BLUE NO. 2; FD&C YELLOW NO. 6; POTASSIUM CHLORIDE; TITANIUM DIOXIDE; SHELLAC; ALCOHOL; METHYL ALCOHOL; BUTYL ALCOHOL; ISOPROPYL ALCOHOL; FERROSOFERRIC OXIDE; WATER; PROPYLENE GLYCOL

HIGHLIGHTS OF PRESCRIBING INFORMATION

These highlights do not include all the information needed to use PRADAXA safely and effectively. See full prescribing information for PRADAXA.
PRADAXA® (dabigatran etexilate mesylate) capsules for oral use
Initial U.S. Approval: 2010

1 INDICATIONS AND USAGE

PRADAXA is a direct thrombin inhibitor indicated to reduce the risk of stroke and systemic embolism in patients with non-valvular atrial fibrillation (1)

2 DOSAGE AND ADMINISTRATION

- For patients with CrCl >30 mL/min: 150 mg orally, twice daily (2.1)
- For patients with CrCl 15-30 mL/min: 75 mg orally, twice daily (2.1)
- Instruct patients not to chew, break, or open capsules (2.1)
- Review recommendations for converting to or from other oral or parenteral anticoagulants (2.2, 2.3)
- Temporarily discontinue PRADAXA before invasive or surgical procedures when possible, then restart promptly (2.4)

3 DOSAGE FORMS AND STRENGTHS

Capsules: 75 mg and 150 mg (3)

4 CONTRAINDICATIONS

- Active pathological bleeding (4)
- History of serious hypersensitivity reaction to PRADAXA (4)

5 WARNINGS AND PRECAUTIONS

- Risk of bleeding: PRADAXA can cause serious and, sometimes, fatal bleeding. Promptly evaluate signs and symptoms of blood loss. (5.1)
- Temporary discontinuation: Avoid lapses in therapy to minimize risk of stroke (5.2)
- P-gp inducers and inhibitors: Avoid coadministration of rifampin with PRADAXA because of effects on dabigatran exposure (5.3)

6 ADVERSE REACTIONS

Most common adverse reactions (>15%) are gastritis-like symptoms and bleeding (6.1)

To report SUSPECTED ADVERSE REACTIONS, contact Boehringer Ingelheim Pharmaceuticals, Inc. at (800) 542-6257 or (800) 459-9906 TTY or FDA at 1-800-FDA-1088 or www.fda.gov/medwatch.

8 USE IN SPECIFIC POPULATIONS

Geriatric use: Risk of bleeding increases with age (8.5)

FULL PRESCRIBING INFORMATION

1 INDICATIONS AND USAGE

PRADAXA is indicated to reduce the risk of stroke and systemic embolism in patients with non-valvular atrial fibrillation.

2 DOSAGE AND ADMINISTRATION

2.1 Recommended Dose

For patients with creatinine clearance (CrCl) >30 mL/min, the recommended dose of PRADAXA is 150 mg taken orally, twice daily, with or without food. For patients with CrCl 15-30 mL/min, the recommended dose is 75 mg twice daily [see Use in Specific Populations (8.6) and Clinical Pharmacology (12.3)]. Dosing recommendations for patients with a CrCL <15 mL/min or on dialysis cannot be provided.

Instruct patients to swallow the capsules whole. Breaking, chewing, or emptying the contents of the capsule can result in increased exposure [see Clinical Pharmacology (12.3)].

If a dose of PRADAXA is not taken at the scheduled time, the dose should be taken as soon as possible on the same day; the missed dose should be skipped if it cannot be taken at least 6 hours before the next scheduled dose. The dose of PRADAXA should not be doubled to make up for a missed dose.

2.2 Converting from or to Warfarin

When converting patients from warfarin therapy to PRADAXA, discontinue warfarin and start PRADAXA when the international normalized ratio (INR) is below 2.0.

When converting from PRADAXA to warfarin, adjust the starting time of warfarin based on creatinine clearance as follows:

- For CrCl >50 mL/min, start warfarin 3 days before discontinuing PRADAXA.
- For CrCl 31-50 mL/min, start warfarin 2 days before discontinuing PRADAXA.
- For CrCl 15-30 mL/min, start warfarin 1 day before discontinuing PRADAXA.
- For CrCl <15 mL/min, no recommendations can be made.

Because PRADAXA can contribute to an elevated INR, the INR will better reflect warfarin’s effect after PRADAXA has been stopped for at least 2 days.

2.3 Converting from or to Parenteral Anticoagulants

For patients currently receiving a parenteral anticoagulant, start PRADAXA 0 to 2 hours before the time that the next dose of the parenteral drug was to have been administered or at the time of discontinuation of a continuously administered parenteral drug (e.g., intravenous unfractionated heparin).

For patients currently taking PRADAXA, wait 12 hours (CrCl ≥30 mL/min) or 24 hours (CrCl <30 mL/min) after the last dose of PRADAXA before initiating treatment with a parenteral anticoagulant [see Clinical Pharmacology (12.3)].

2.4 Surgery and Interventions

If possible, discontinue PRADAXA 1 to 2 days (CrCl ≥50 mL/min) or 3 to 5 days (CrCl <50 mL/min) before invasive or surgical procedures because of the increased risk of bleeding. Consider longer times for patients undergoing major surgery, spinal puncture, or placement of a spinal or epidural catheter or port, in whom complete hemostasis may be required [see Use in Specific Populations (8.6) and Clinical Pharmacology (12.3)].

If surgery cannot be delayed, there is an increased risk of bleeding [see Warnings and Precautions (5.1)]. This risk of bleeding should be weighed against the urgency of intervention [see Warnings and Precautions (5.2)]. Bleeding risk can be assessed by the ecarin clotting time (ECT). This test is a better marker of the anticoagulant activity of dabigatran than activated partial thromboplastin time (aPTT), prothrombin time (PT)/INR, or thrombin time (TT). If ECT is not available, the aPTT test provides an approximation of PRADAXA’s anticoagulant activity [see Clinical Pharmacology (12.2)].

3 DOSAGE FORMS AND STRENGTHS

Capsules with a light blue opaque cap imprinted in black with the Boehringer Ingelheim company symbol and a cream-colored opaque body imprinted in black with "R150" (150 mg) or "R75" (75 mg).

4 CONTRAINDICATIONS

PRADAXA is contraindicated in patients with:

- Active pathological bleeding [see Warnings and Precautions (5.1) and Adverse Reactions (6.1)].
- History of a serious hypersensitivity reaction to PRADAXA (e.g., anaphylactic reaction or anaphylactic shock) [see Adverse Reactions (6.1)].

5 WARNINGS AND PRECAUTIONS

5.1 Risk of Bleeding

PRADAXA increases the risk of bleeding and can cause significant and, sometimes, fatal bleeding. Risk factors for bleeding include the use of drugs that increase the risk of bleeding in general (e.g., anti-platelet agents, heparin, fibrinolytic therapy, and chronic use of NSAIDs) and labor and delivery. Promptly evaluate any signs or symptoms of blood loss (e.g., a drop in hemoglobin and/or hematocrit or hypotension). Discontinue PRADAXA in patients with active pathological bleeding.

In the RE-LY (Randomized Evaluation of Long-term Anticoagulant Therapy) study, a life-threatening bleed (bleeding that met one or more of the following criteria: fatal, symptomatic intracranial, reduction in hemoglobin of at least 5 grams per deciliter, transfusion of at least 4 units of blood, associated with hypotension requiring the use of intravenous inotropic agents, or necessitating surgical intervention) occurred at an annualized rate of 1.5% and 1.8% for PRADAXA 150 mg and warfarin, respectively [see Adverse Reactions (6.1)].

5.2 Temporary Discontinuation of PRADAXA

Discontinuing anticoagulants, including PRADAXA, for active bleeding, elective surgery, or invasive procedures places patients at an increased risk of stroke. Lapses in therapy should be avoided, and if anticoagulation with PRADAXA must be temporarily discontinued for any reason, therapy should be restarted as soon as possible.

5.3 Effect of P-gp Inducers and Inhibitors on Dabigatran Exposure

The concomitant use of PRADAXA with P-gp inducers (e.g., rifampin) reduces exposure to dabigatran and should generally be avoided [see Clinical Pharmacology (12.3)].

P-gp inhibitors ketoconazole, verapamil, amiodarone, quinidine, and clarithromycin do not require dose adjustments. These results should not be extrapolated to other P-gp inhibitors [see Clinical Pharmacology (12.3)].

6 ADVERSE REACTIONS

6.1 Clinical Trials Experience

The RE-LY study provided safety information on the use of two doses of PRADAXA and warfarin [see Clinical Studies (14)]. The numbers of patients and their exposures are described in Table 1. Limited information is presented on the 110 mg dosing arm because this dose is not approved.

Table 1 Summary of Treatment Exposure in RE-LY
 | PRADAXA 110 mg twice daily | PRADAXA 150 mg twice daily | Warfarin
Total number treated | 5983 | 6059 | 5998
Exposure
> 12 months | 4936 | 4939 | 5193
> 24 months | 2387 | 2405 | 2470
Mean exposure (months) | 20.5 | 20.3 | 21.3
Total patient-years | 10,242 | 10,261 | 10,659

Because clinical studies are conducted under widely varying conditions and over varying lengths of time, adverse reaction rates observed in the clinical studies of a drug cannot be directly compared to rates in the clinical studies of another drug and may not reflect the rates observed in practice.

Drug Discontinuation in RE-LY

The rates of adverse reactions leading to treatment discontinuation were 21% for PRADAXA 150 mg and 16% for warfarin. The most frequent adverse reactions leading to discontinuation of PRADAXA were bleeding and gastrointestinal events (i.e., dyspepsia, nausea, upper abdominal pain, gastrointestinal hemorrhage, and diarrhea).

Bleeding [see Warnings and Precautions (5.1)]

Table 2 shows the number of patients experiencing serious bleeding during the treatment period in the RE-LY study, with the bleeding rate per 100 patient-years (%). Major bleeds fulfilled one or more of the following criteria: bleeding associated with a reduction in hemoglobin of at least 2 grams per deciliter or leading to a transfusion of at least 2 units of blood, or symptomatic bleeding in a critical area or organ (intraocular, intracranial, intraspinal or intramuscular with compartment syndrome, retroperitoneal bleeding, intra-articular bleeding, or pericardial bleeding). A life-threatening bleed met one or more of the following criteria: fatal, symptomatic intracranial bleed, reduction in hemoglobin of at least 5 grams per deciliter, transfusion of at least 4 units of blood, associated with hypotension requiring the use of intravenous inotropic agents, or necessitating surgical intervention. Intracranial hemorrhage included intracerebral (hemorrhagic stroke), subarachnoid, and subdural bleeds.

Table 2 Bleeding Events* (per 100 Patient-Years)
 | PRADAXA 150 mg twice daily N (%) | Warfarin N (%) | Hazard Ratio (95% CI**)
Randomized patients | 6076 | 6022
Patient-years | 12,033 | 11,794
Intracranial hemorrhage | 38 (0.3) | 90 (0.8) | 0.41 (0.28, 0.60)
Life-threatening bleed | 179 (1.5) | 218 (1.9) | 0.80 (0.66, 0.98)
Major bleed | 399 (3.3) | 421 (3.6) | 0.93 (0.81, 1.07)
Any bleed | 1993 (16.6) | 2166 (18.4) | 0.91 (0.85, 0.96)
* Patients contributed multiple events and events were counted in multiple categories.
** Confidence interval

The risk of major bleeds was similar with PRADAXA 150 mg and warfarin across major subgroups defined by baseline characteristics, with the exception of age, where there was a trend towards a higher incidence of major bleeding on PRADAXA (hazard ratio 1.2, 95% CI: 1.0 to 1.4) for patients ≥75 years of age.

There was a higher rate of major gastrointestinal bleeds in patients receiving PRADAXA 150 mg than in patients receiving warfarin (1.6% vs. 1.1%, respectively, with a hazard ratio vs. warfarin of 1.5, 95% CI, 1.2 to 1.9), and a higher rate of any gastrointestinal bleeds (6.1% vs. 4.0%, respectively).

Gastrointestinal Adverse Reactions

Patients on PRADAXA 150 mg had an increased incidence of gastrointestinal adverse reactions (35% vs. 24% on warfarin). These were commonly dyspepsia (including abdominal pain upper, abdominal pain, abdominal discomfort, and epigastric discomfort) and gastritis-like symptoms (including GERD, esophagitis, erosive gastritis, gastric hemorrhage, hemorrhagic gastritis, hemorrhagic erosive gastritis, and gastrointestinal ulcer).

Hypersensitivity Reactions

In the RE-LY study, drug hypersensitivity (including urticaria, rash, and pruritus), allergic edema, anaphylactic reaction, and anaphylactic shock were reported in <0.1% of patients receiving PRADAXA.

7 DRUG INTERACTIONS

The concomitant use of PRADAXA with P-gp inducers (e.g., rifampin) reduces exposure to dabigatran and should generally be avoided [see Clinical Pharmacology (12.3)].

P-gp inhibitors ketoconazole, verapamil, amiodarone, quinidine, and clarithromycin do not require dose adjustments. These results should not be extrapolated to other P-gp inhibitors [see Clinical Pharmacology (12.3)].

8 USE IN SPECIFIC POPULATIONS

8.1 Pregnancy

Pregnancy Category C

There are no adequate and well-controlled studies in pregnant women.

Dabigatran has been shown to decrease the number of implantations when male and female rats were treated at a dosage of 70 mg/kg (about 2.6 to 3.0 times the human exposure at maximum recommended human dose [MRHD] of 300 mg/day based on area under the curve [AUC] comparisons) prior to mating and up to implantation (gestation Day 6). Treatment of pregnant rats after implantation with dabigatran at the same dose increased the number of dead offspring and caused excess vaginal/uterine bleeding close to parturition. Although dabigatran increased the incidence of delayed or irregular ossification of fetal skull bones and vertebrae in the rat, it did not induce major malformations in rats or rabbits.

8.2 Labor and Delivery

Safety and effectiveness of PRADAXA during labor and delivery have not been studied in clinical trials. Consider the risks of bleeding and of stroke in using PRADAXA in this setting [see Warnings and Precautions (5.1)].

Death of offspring and mother rats during labor in association with uterine bleeding occurred during treatment of pregnant rats from implantation (gestation Day 7) to weaning (lactation Day 21) with dabigatran at a dose of 70 mg/kg (about 2.6 times the human exposure at MRHD of 300 mg/day based on AUC comparisons).

8.3 Nursing Mothers

It is not known whether dabigatran is excreted in human milk. Because many drugs are excreted in human milk, caution should be exercised when PRADAXA is administered to a nursing woman.

8.4 Pediatric Use

Safety and effectiveness of PRADAXA in pediatric patients has not been established.

8.5 Geriatric Use

Of the total number of patients in the RE-LY study, 82% were 65 and over, while 40% were 75 and over. The risk of stroke and bleeding increases with age, but the risk-benefit profile is favorable in all age groups [see Warnings and Precautions (5), Adverse Reactions (6.1), and Clinical Studies (14)].

8.6 Renal Impairment

No dose adjustment of PRADAXA is recommended in patients with mild or moderate renal impairment. Reduce the dose of PRADAXA in patients with severe renal impairment (CrCl 15-30 mL/min) [see Dosage and Administration (2.1)]. Dosing recommendations for patients with CrCl <15 mL/min or on dialysis cannot be provided.

10 OVERDOSAGE

Accidental overdose may lead to hemorrhagic complications. There is no antidote to dabigatran etexilate or dabigatran. In the event of hemorrhagic complications, initiate appropriate clinical support, discontinue treatment with PRADAXA, and investigate the source of bleeding. Dabigatran is primarily excreted in the urine; therefore, maintain adequate diuresis. Dabigatran can be dialyzed (protein binding is low), with the removal of about 60% of drug over 2 to 3 hours; however, data supporting this approach are limited. Consider surgical hemostasis or the transfusion of fresh frozen plasma or red blood cells. There is some experimental evidence to support the role of activated prothrombin complex concentrates (e.g., FEIBA), or recombinant Factor VIIa, or concentrates of coagulation factors II, IX or X; however, their usefulness in clinical settings has not been established. Consider administration of platelet concentrates in cases where thrombocytopenia is present or long-acting antiplatelet drugs have been used. Measurement of aPTT or ECT may help guide therapy [see Clinical Pharmacology (12.2)].

11 DESCRIPTION

The chemical name for dabigatran etexilate mesylate, a direct thrombin inhibitor, is β-Alanine, N-[[2-[[[4-[[[(hexyloxy)carbonyl]amino]iminomethyl] phenyl]amino]methyl]-1-methyl-1H-benzimidazol-5-yl]carbonyl]-N-2-pyridinyl-,ethyl ester, methanesulfonate. The empirical formula is C34H41N7O5 • CH4O3S and the molecular weight is 723.86 (mesylate salt), 627.75 (free base). The structural formula is:

Dabigatran etexilate mesylate is a yellow-white to yellow powder. A saturated solution in pure water has a solubility of 1.8 mg/mL. It is freely soluble in methanol, slightly soluble in ethanol, and sparingly soluble in isopropanol.

The 150 mg capsule for oral administration contains 172.95 mg dabigatran etexilate mesylate, which is equivalent to 150 mg of dabigatran etexilate, and the following inactive ingredients: acacia, dimethicone, hypromellose, hydroxypropyl cellulose, talc, and tartaric acid. The capsule shell is composed of carrageenan, FD&C Blue No. 2, FD&C Yellow No. 6, hypromellose, potassium chloride, titanium dioxide, and black edible ink. The 75 mg capsule contains 86.48 mg dabigatran etexilate mesylate, equivalent to 75 mg dabigatran etexilate, and is otherwise similar to the 150 mg capsule.

12 CLINICAL PHARMACOLOGY

12.1 Mechanism of Action

Dabigatran and its acyl glucuronides are competitive, direct thrombin inhibitors. Because thrombin (serine protease) enables the conversion of fibrinogen into fibrin during the coagulation cascade, its inhibition prevents the development of a thrombus. Both free and clot-bound thrombin, and thrombin-induced platelet aggregation are inhibited by the active moieties.

12.2 Pharmacodynamics

At recommended therapeutic doses, dabigatran etexilate prolongs the aPTT, ECT, and TT. With an oral dose of 150 mg twice daily the median peak aPTT is approximately 2x control. Twelve hours after the last dose the median aPTT is 1.5x control, with less than 10% of patients exceeding 2x control. In the RE-LY trial, the median (10th to 90th percentile) trough aPTT in patients receiving the 150 mg dose was 52 (40 to 76) seconds. The median (10th to 90th percentile) trough ECT in patients receiving the 150 mg dose was 63 (44 to 103) seconds. The INR test is relatively insensitive to the activity of dabigatran and may or may not be elevated in patients on PRADAXA. When converting a patient from PRADAXA to warfarin therapy, the INR is unlikely to be useful until at least 2 days after discontinuation of PRADAXA.

Cardiac Electrophysiology

No prolongation of the QTc interval was observed with dabigatran etexilate at doses up to 600 mg.

12.3 Pharmacokinetics

Dabigatran etexilate mesylate is absorbed as the dabigatran etexilate ester. The ester is then hydrolyzed, forming dabigatran, the active moiety. Dabigatran is metabolized to four different acyl glucuronides and both the glucuronides and dabigatran have similar pharmacological activity. Pharmacokinetics described here refer to the sum of dabigatran and its glucuronides. Dabigatran displays dose-proportional pharmacokinetics in healthy subjects and patients in the range of doses from 10 to 400 mg.

Absorption

The absolute bioavailability of dabigatran following oral administration of dabigatran etexilate is approximately 3 to 7%. Dabigatran etexilate is a substrate of the efflux transporter P-gp. After oral administration of dabigatran etexilate in healthy volunteers, Cmax occurs at 1 hour post-administration in the fasted state. Coadministration of PRADAXA with a high-fat meal delays the time to Cmax by approximately 2 hours but has no effect on the bioavailability of dabigatran; PRADAXA may be administered with or without food.

The oral bioavailability of dabigatran etexilate increases by 75% when the pellets are taken without the capsule shell compared to the intact capsule formulation. PRADAXA capsules should therefore not be broken, chewed, or opened before administration.

Distribution

Dabigatran is approximately 35% bound to human plasma proteins. The red blood cell to plasma partitioning of dabigatran measured as total radioactivity is less than 0.3. The volume of distribution of dabigatran is 50 to 70 L. Dabigatran pharmacokinetics are dose proportional after single doses of 10 to 400 mg. Given twice daily, dabigatran’s accumulation factor is approximately two.

Elimination

Dabigatran is eliminated primarily in the urine. Renal clearance of dabigatran is 80% of total clearance after intravenous administration. After oral administration of radiolabeled dabigatran, 7% of radioactivity is recovered in urine and 86% in feces. The half-life of dabigatran in healthy subjects is 12 to 17 hours.

Metabolism

After oral administration, dabigatran etexilate is converted to dabigatran. The cleavage of the dabigatran etexilate by esterase-catalyzed hydrolysis to the active principal dabigatran is the predominant metabolic reaction. Dabigatran is not a substrate, inhibitor, or inducer of CYP450 enzymes. Dabigatran is subject to conjugation forming pharmacologically active acyl glucuronides. Four positional isomers, 1-O, 2-O, 3-O, and 4-O-acylglucuronide exist, and each accounts for less than 10% of total dabigatran in plasma.

Renal Impairment

An open, parallel-group single-center study compared dabigatran pharmacokinetics in healthy subjects and patients with mild to moderate renal impairment receiving a single dose of PRADAXA 150 mg. Based on pharmacokinetic modeling, estimated exposure to dabigatran increases with the severity of renal function impairment (Table 3). Similar findings were observed in the RE-LY trial.

Table 3 Estimated Pharmacokinetic Parameters of Dabigatran by Renal Function
Renal Function | CrCl (mL/min) | Increase in AUC | Increase in Cmax | t1/2 (h)
Normal | 80 | 1x | 1x | 13
Mild | 50 | 1.5x | 1.1x | 15
Moderate | 30 | 3.2x | 1.7x | 18

Hepatic Impairment

Administration of PRADAXA in patients with moderate hepatic impairment (Child-Pugh B) showed a large inter-subject variability, but no evidence of a consistent change in exposure or pharmacodynamics.

Drug Interactions

Impact of Other Drugs on Dabigatran

P-gp Inducers

Rifampin: Rifampin 600 mg once daily for 7 days followed by a single dose of dabigatran decreased its AUC and Cmax by 66% and 67%, respectively. By Day 7 after cessation of rifampin treatment, dabigatran exposure was close to normal [see Warnings and Precautions (5.3) and Drug Interactions (7)].

P-gp Inhibitors

In studies with the P-gp inhibitors ketoconazole, amiodarone, verapamil, and quinidine, the time to peak, terminal half-life, and mean residence time of dabigatran were not affected. Any observed changes in Cmax and AUC are described below.

Dronedarone: Exposure to dabigatran is higher when it is administered with dronedarone than when it is administered alone (1.7- to 2-fold).

Ketoconazole: Ketoconazole increased dabigatran AUC0-∞ and Cmax values by 138% and 135%, respectively, after a single dose of 400 mg, and 153%, and 149%, respectively, after multiple daily doses of 400 mg.

Verapamil: When dabigatran etexilate was coadministered with oral verapamil, the Cmax and AUC of dabigatran were increased. The extent of increase depends on the formulation of verapamil and timing of administration. If verapamil is present in the gut when dabigatran is taken, it will increase exposure to dabigatran with the greatest increase observed when a single dose of immediate-release verapamil is given one hour prior to dabigatran (AUC increased by a factor of 2.4). If verapamil is given 2 hours after dabigatran, the increase in AUC is negligible. In the population pharmacokinetics study from RE-LY, no important changes in dabigatran trough levels were observed in patients who received verapamil.

Amiodarone: When dabigatran etexilate was coadministered with a single 600 mg oral dose of amiodarone, the dabigatran AUC and Cmax increased by 58% and 50%, respectively. The increase in exposure was mitigated by a 65% increase in the renal clearance of dabigatran in the presence of amiodarone. The increase in renal clearance may persist after amiodarone is discontinued because of amiodarone’s long half-life. In the population pharmacokinetics study from RE-LY, no important changes in dabigatran trough levels were observed in patients who received amiodarone.

Quinidine: Quinidine was given as 200 mg dose every 2 hours up to a total dose of 1000 mg. Dabigatran etexilate was given over 3 consecutive days, the last evening dose on Day 3 with or without quinidine pre-dosing. Concomitant quinidine administration increased dabigatran’s AUC and Cmax by 53% and 56%, respectively.

Clarithromycin: Coadministered clarithromycin had no impact on the exposure to dabigatran.

Other Drugs

Clopidogrel: When dabigatran etexilate was given concomitantly with a loading dose of 300 mg or 600 mg clopidogrel, the dabigatran AUC and Cmax increased by approximately 30% and 40%, respectively. The concomitant administration of dabigatran etexilate and clopidogrel resulted in no further prolongation of capillary bleeding times compared to clopidogrel monotherapy. When comparing combined treatment and the respective mono-treatments, the coagulation measures for dabigatran’s effect (aPTT, ECT, and TT) remained unchanged, and inhibition of platelet aggregation (IPA), a measurement of clopidogrel’s effect, remained unchanged.

Enoxaparin: Enoxaparin 40 mg given subcutaneously for 3 days with the last dose given 24 hours before a single dose of PRADAXA had no impact on the exposure to dabigatran or the coagulation measures aPTT, ECT, or TT.

Diclofenac, Ranitidine, and Digoxin: None of these drugs alters exposure to dabigatran.

In RE-LY, dabigatran plasma samples were also collected. The concomitant use of proton pump inhibitors, H2 antagonists, and digoxin did not appreciably change the trough concentration of dabigatran.

Impact of Dabigatran on Other Drugs

In clinical studies exploring CYP3A4, CYP2C9, P-gp and other pathways, dabigatran did not meaningfully alter the pharmacokinetics of amiodarone, atorvastatin, clarithromycin, diclofenac, clopidogrel, digoxin, pantoprazole, or ranitidine.

13 NONCLINICAL TOXICOLOGY

13.1 Carcinogenesis, Mutagenesis, Impairment of Fertility

Dabigatran was not carcinogenic when administered by oral gavage to mice and rats for up to 2 years. The highest doses tested (200 mg/kg/day) in mice and rats were approximately 3.6 and 6 times, respectively, the human exposure at MRHD of 300 mg/day based on AUC comparisons.

Dabigatran was not mutagenic in in vitro tests, including bacterial reversion tests, mouse lymphoma assay and chromosomal aberration assay in human lymphocytes, and the in vivo micronucleus assay in rats.

In the rat fertility study with oral gavage doses of 15, 70, and 200 mg/kg, males were treated for 29 days prior to mating, during mating up to scheduled termination, and females were treated 15 days prior to mating through gestation Day 6. No adverse effects on male or female fertility were observed at 200 mg/kg or 9 to 12 times the human exposure at MRHD of 300 mg/day based on AUC comparisons. However, the number of implantations decreased in females receiving 70 mg/kg, or 3 times the human exposure at MRHD based on AUC comparisons.

14 CLINICAL STUDIES

The clinical evidence for the efficacy of PRADAXA was derived from RE-LY (Randomized Evaluation of Long-term Anticoagulant Therapy), a multi-center, multi-national, randomized parallel group trial comparing two blinded doses of PRADAXA (110 mg twice daily and 150 mg twice daily) with open-label warfarin (dosed to target INR of 2 to 3) in patients with non-valvular, persistent, paroxysmal, or permanent atrial fibrillation and one or more of the following additional risk factors:

- Previous stroke, transient ischemic attack (TIA), or systemic embolism
- Left ventricular ejection fraction <40%
- Symptomatic heart failure, ≥ New York Heart Association Class 2
- Age ≥75 years
- Age ≥65 years and one of the following: diabetes mellitus, coronary artery disease (CAD), or hypertension

The primary objective of this study was to determine if PRADAXA was non-inferior to warfarin in reducing the occurrence of the composite endpoint, stroke (ischemic and hemorrhagic) and systemic embolism. The study was designed to ensure that PRADAXA preserved more than 50% of warfarin’s effect as established by previous randomized, placebo-controlled trials of warfarin in atrial fibrillation. Statistical superiority was also analyzed.

A total of 18,113 patients were randomized and followed for a median of 2 years. The patient’s mean age was 71.5 years and the mean CHADS2 score was 2.1. The patient population was 64% male, 70% Caucasian, 16% Asian, and 1% black. Twenty percent of patients had a history of a stroke or TIA and 50% were Vitamin K antagonist (VKA) naïve, defined as less than 2 months total lifetime exposure to a VKA. Thirty-two percent of the population had never been exposed to a VKA. Concomitant diseases of patients in this trial included hypertension 79%, diabetes 23%, and CAD 28%. At baseline, 40% of patients were on aspirin and 6% were on clopidogrel. For patients randomized to warfarin, the mean percentage of time in therapeutic range (INR 2 to 3) was 64%; the mean percentages of time INR measurements were greater than 4 or less than 1.5 were 2% and 5%, respectively.

Relative to warfarin and to PRADAXA 110 mg twice daily, PRADAXA 150 mg twice daily significantly reduced the primary composite endpoint of stroke and systemic embolism (see Table 4 and Figure 1).

Table 4 First Occurrence of Stroke or Systemic Embolism in the RE-LY Study
 | PRADAXA 150 mg twice daily | PRADAXA 110 mg twice daily | Warfarin
Patients randomized | 6076 | 6015 | 6022
Patients (%) with events | 134 (2.2%) | 183 (3%) | 202 (3.4%)
Hazard ratio vs. warfarin (95% CI) | 0.65 (0.52, 0.81) | 0.90 (0.74, 1.10)
P-value for superiority | 0.0001 | 0.3
Hazard ratio vs. PRADAXA 110 mg (95% CI) | 0.72 (0.58, 0.90)
P-value for superiority | 0.004

Figure 1 Kaplan-Meier Curve Estimate of Time to First Stroke or Systemic Embolism

The contributions of the components of the composite endpoint, including stroke by subtype, are shown in Table 5. The treatment effect was primarily a reduction in stroke. PRADAXA 150 mg twice daily significantly reduced both ischemic and hemorrhagic strokes relative to warfarin.

Table 5 Strokes and Systemic Embolism in the RE-LY Study
 | PRADAXA 150 mg twice daily | Warfarin | Hazard ratio vs. warfarin (95% CI)
Patients randomized | 6076 | 6022
Stroke | 122 | 186 | 0.64 (0.51, 0.81)
Ischemic stroke | 103 | 134 | 0.75 (0.58, 0.97)
Hemorrhagic stroke | 12 | 45 | 0.26 (0.14, 0.49)
Systemic embolism | 13 | 21 | 0.61 (0.30, 1.21)

The efficacy of PRADAXA 150 mg twice daily was generally consistent across major subgroups (see Figure 2).

Figure 2 Stroke and Systemic Embolism Hazard Ratios by Baseline Characteristics

Centers were ranked post hoc by the percentage of time that warfarin-treated patients were in therapeutic range (INR 2 to 3). Findings for stroke/systemic embolism, all-cause mortality, and major bleeds are shown for centers above and below the median level of INR control in Table 6. The benefits of PRADAXA 150 mg relative to warfarin were most apparent in patients enrolled at centers with INR control below the median.

Table 6 Center INR Control in the RE-LY Study
 | Centers with INR control below the median of 67% | Centers with INR control above the median of 67%
Stroke/systemic embolism | 0.57 (0.42, 0.76) | 0.76 (0.55, 1.05)
All-cause mortality | 0.78 (0.66, 0.93) | 1.01 (0.84, 1.23)
Major bleed | 0.82 (0.68, 0.99) | 1.08 (0.89, 1.31)

The risk of myocardial infarction was numerically greater in patients who received PRADAXA (1.5% for 150 mg dose) than in those who received warfarin (1.1%).

16 HOW SUPPLIED/STORAGE AND HANDLING

PRADAXA 75 mg capsules have a light blue opaque cap imprinted with the Boehringer Ingelheim company symbol and a cream-colored opaque body imprinted with "R75". The color of the imprinting is black. The capsules are supplied in the packages listed:

- NDC 0597-0107-54 Unit of use bottle of 60 capsules
- NDC 0597-0107-60 Blister package containing 60 capsules (10 x 6 capsule blister cards)

PRADAXA 150 mg capsules have a light blue opaque cap imprinted with the Boehringer Ingelheim company symbol and a cream-colored opaque body imprinted with "R150". The color of the imprinting is black. The capsules are supplied in the packages listed:

- NDC 0597-0135-54 Unit of use bottle of 60 capsules
- NDC 0597-0135-60 Blister package containing 60 capsules (10 x 6 capsule blister cards)

Bottles

Store at 25°C (77°F); excursions permitted to 15°-30°C (59°-86°F). Once opened, the product must be used within 30 days. Keep the bottle tightly closed. Store in the original package to protect from moisture.

Blisters

Store at 25°C (77°F); excursions permitted to 15°-30°C (59°-86°F). Store in the original package to protect from moisture.

Keep out of the reach of children.

17 PATIENT COUNSELING INFORMATION

See Medication Guide

17.1 Instructions for Patients

- Tell patients to take PRADAXA exactly as prescribed.
- Remind patients not to discontinue PRADAXA without talking to the health care provider who prescribed it.
- Advise patients not to chew or break the capsules before swallowing them and not to open the capsules and take the pellets alone (e.g., sprinkled over food or into beverages).

17.2 Bleeding

Inform patients that they may bleed more easily, may bleed longer, and should call their health care provider for any signs or symptoms of bleeding.

Instruct patients to seek emergency care right away if they have any of the following, which may be a sign or symptom of serious bleeding:

- Unusual bruising (bruises that appear without known cause or that get bigger)
- Pink or brown urine
- Red or black, tarry stools
- Coughing up blood
- Vomiting blood, or vomit that looks like coffee grounds

Instruct patients to call their health care provider or to get prompt medical attention if they experience any signs or symptoms of bleeding:

- Pain, swelling or discomfort in a joint
- Headaches, dizziness, or weakness
- Reoccurring nose bleeds
- Unusual bleeding from gums
- Bleeding from a cut that takes a long time to stop
- Menstrual bleeding or vaginal bleeding that is heavier than normal

17.3 Gastrointestinal Adverse Reactions

Instruct patients to call their health care provider if they experience any signs or symptoms of dyspepsia or gastritis:

- Dyspepsia (upset stomach), burning, or nausea
- Abdominal pain or discomfort
- Epigastric discomfort, GERD (gastric indigestion)

17.4 Invasive or Surgical Procedures

Instruct patients to inform their health care provider that they are taking PRADAXA before any invasive procedure (including dental procedures) is scheduled.

17.5 Concomitant Medications

Ask patients to list all prescription medications, over-the-counter medications, or dietary supplements they are taking or plan to take so their health care provider knows about other treatments that may affect bleeding risk (e.g., aspirin or NSAIDs) or dabigatran exposure.

Distributed by:
Boehringer Ingelheim Pharmaceuticals, Inc.
Ridgefield, CT 06877 USA

Copyright 2011 Boehringer Ingelheim Pharmaceuticals, Inc.
ALL RIGHTS RESERVED

75461-02
IT5060BC072011

75457-02
IT5400B

MEDICATION GUIDE
PRADAXA (pra dax´ a)
(dabigatran etexilate mesylate)
capsules

Read this Medication Guide before you start taking PRADAXA and each time you get a refill. There may be new information. This Medication Guide does not take the place of talking with your doctor about your medical condition or your treatment.

What is the most important information I should know about PRADAXA?

- PRADAXA can cause bleeding which can be serious, and sometimes lead to death. This is because PRADAXA is a blood thinner medicine that lowers the chance of blood clots forming in your body.
- You may have a higher risk of bleeding if you take PRADAXA and:
  - are over 75 years old
  - have kidney problems
  - have stomach or intestine bleeding that is recent or keeps coming back, or you have a stomach ulcer
  - take other medicines that increase your risk of bleeding, including: Tell your doctor if you take any of these medicines. Ask your doctor or pharmacist if you are not sure if your medicine is one listed above.
    - aspirin or aspirin containing products
    - long-term (chronic) use of non-steroidal anti-inflammatory drugs (NSAIDs)
    - warfarin sodium (Coumadin®, Jantoven®)
    - a medicine that contains heparin
    - clopidogrel (Plavix®)
    - prasugrel (Effient®)
- PRADAXA can increase your risk of bleeding because it lessens the ability of your blood to clot. While you take PRADAXA:
  Call your doctor or get medical help right away if you have any of these signs or symptoms of bleeding:
  Take PRADAXA exactly as prescribed. Do not stop taking PRADAXA without first talking to the doctor who prescribes it for you. Stopping PRADAXA may increase your risk of a stroke.
  PRADAXA may need to be stopped, if possible, for one or more days before any surgery, or medical or dental procedure. If you need to stop taking PRADAXA for any reason, talk to the doctor who prescribed PRADAXA for you to find out when you should stop taking it. Your doctor will tell you when to start taking PRADAXA again after your surgery or procedure.
  See "What are the possible side effects of PRADAXA?" for more information about side effects.
  - you may bruise more easily
  - it may take longer for any bleeding to stop

What is PRADAXA?

PRADAXA is a prescription medicine used to reduce the risk of stroke and blood clots in people who have a medical condition called atrial fibrillation. With atrial fibrillation, part of the heart does not beat the way it should. This can lead to blood clots forming and increase your risk of a stroke. PRADAXA is a blood thinner medicine that lowers the chance of blood clots forming in your body.

It is not known if PRADAXA is safe and works in children.

Who should not take PRADAXA?

Do not take PRADAXA if you:

- currently have certain types of abnormal bleeding. Talk to your doctor, before taking PRADAXA if you currently have unusual bleeding.
- have had a serious allergic reaction to PRADAXA. Ask your doctor if you are not sure.

What should I tell my doctor before taking PRADAXA?

Before you take PRADAXA, tell your doctor if you:

- have kidney problems
- have ever had bleeding problems
- have ever had stomach ulcers
- have any other medical condition
- are pregnant or plan to become pregnant. It is not known if PRADAXA will harm your unborn baby.
- are breastfeeding or plan to breastfeed. It is not known if PRADAXA passes into your breast milk.
  Tell all of your doctors and dentists that you are taking PRADAXA. They should talk to the doctor who prescribed PRADAXA for you, before you have any surgery, or medical or dental procedure.
  Tell your doctor about all the medicines you take, including prescription and non-prescription medicines, vitamins, and herbal supplements. Some of your other medicines may affect the way PRADAXA works. Certain medicines may increase your risk of bleeding. See "What is the most important information I should know about PRADAXA?"
  Especially tell your doctor if you take:
  Know the medicines you take. Keep a list of them and show it to your doctor and pharmacist when you get a new medicine.
  - rifampin (Rifater, Rifamate, Rimactane, Rifadin)

How should I take PRADAXA?

- Take PRADAXA exactly as prescribed by your doctor.
- Do not take PRADAXA more often than your doctor tells you to.
- You can take PRADAXA with or without food.
- Swallow PRADAXA capsules whole. Do not break, chew, or empty the pellets from the capsule.
- If you miss a dose of PRADAXA, take it as soon as you remember. If your next dose is less than 6 hours away, skip the missed dose. Do not take two doses of PRADAXA at the same time.
- Your doctor will decide how long you should take PRADAXA. Do not stop taking PRADAXA without first talking with your doctor. Stopping PRADAXA may increase your risk of stroke.
- Do not run out of PRADAXA. Refill your prescription before you run out. If you plan to have surgery, or a medical or a dental procedure, tell your doctor and dentist that you are taking PRADAXA. You may have to stop taking PRADAXA for a short time. See "What is the most important information I should know about PRADAXA?"
- If you take too much PRADAXA, go to the nearest hospital emergency room or call your doctor or the Poison Control Center right away.

What are the possible side effects of PRADAXA?

PRADAXA can cause serious side effects.

- See "What is the most important information I should know about PRADAXA?"
- Allergic Reactions. In some people, PRADAXA can cause symptoms of an allergic reaction, including hives, rash, and itching. Tell your doctor or get medical help right away if you get any of the following symptoms of a serious allergic reaction with PRADAXA:
  - chest pain or chest tightness
  - swelling of your face or tongue
  - trouble breathing or wheezing
  - feeling dizzy or faint

Common side effects of PRADAXA include:

- indigestion, upset stomach, or burning
- stomach pain

Tell your doctor if you have any side effect that bothers you or that does not go away.

These are not all of the possible side effects of PRADAXA. For more information, ask your doctor or pharmacist.

Call your doctor for medical advice about side effects. You may report side effects to FDA at 1-800-FDA-1088.

How should I store PRADAXA?

- Store PRADAXA at room temperature between 59°F to 86°F (15°C to 30°C). After opening the bottle, use PRADAXA within 30 days. Safely throw away any unused PRADAXA after 30 days.
- Store PRADAXA in the original package to keep it dry. Keep the bottle tightly closed.

Keep PRADAXA and all medicines out of the reach of children.

General information about PRADAXA

Medicines are sometimes prescribed for purposes other than those listed in a Medication Guide. Do not use PRADAXA for a condition for which it was not prescribed. Do not give your PRADAXA to other people, even if they have the same symptoms. It may harm them.

This Medication Guide summarizes the most important information about PRADAXA. If you would like more information, talk with your doctor. You can ask your pharmacist or doctor for information about PRADAXA that is written for health professionals.

For more information, go to www.PRADAXA.com or call 1-800-542-6257 or (TTY) 1-800-459-9906.

What are the ingredients in PRADAXA?

Active ingredient: dabigatran etexilate mesylate

Inactive ingredients: acacia, dimethicone, hypromellose, hydroxypropyl cellulose, talc, and tartaric acid. The capsule shell is composed of carrageenan, FD&C Blue No. 2, FD&C Yellow No. 6, hypromellose, potassium chloride, titanium dioxide, and black edible ink.

Distributed by:
Boehringer Ingelheim Pharmaceuticals, Inc.
Ridgefield, CT 06877 USA

Revised: March 2011
This Medication Guide has been approved by the U.S. Food and Drug Administration.

Copyright 2011 Boehringer Ingelheim Pharmaceuticals, Inc.
ALL RIGHTS RESERVED

75461-02
IT5060BC072011

75457-02
IT5400B

Repackaged by

Rebel Distributors Corp

Thousand Oaks, CA 91320

Coumadin® is a registered trademark for Bristol-Myers Squibb
Jantoven® is a registered trademark for USL Pharma
Plavix® is a registered trademark of sanofi aventis
Effient® is a registered trademark of Eli Lilly and Company